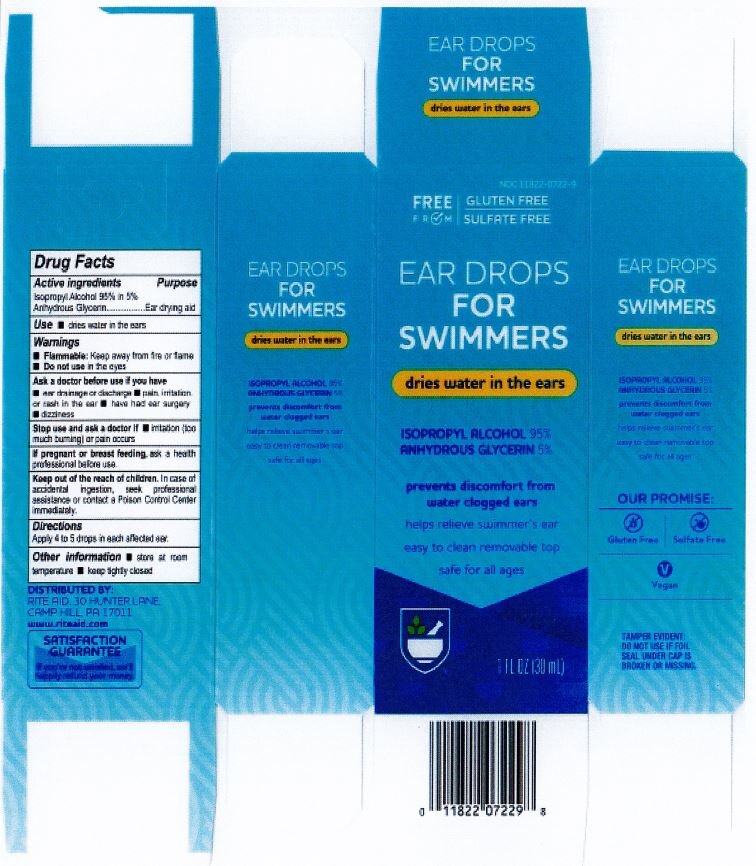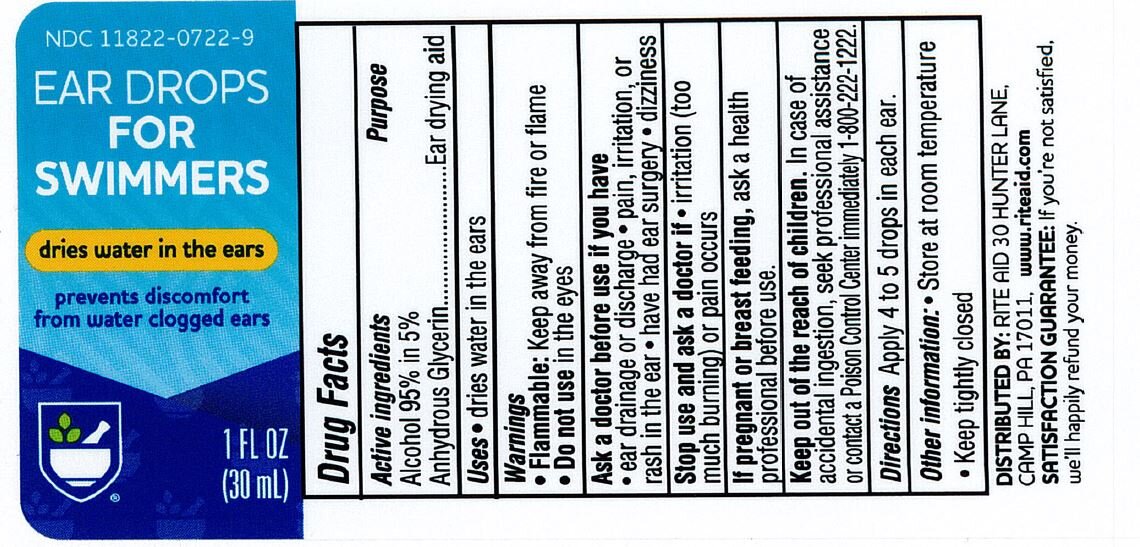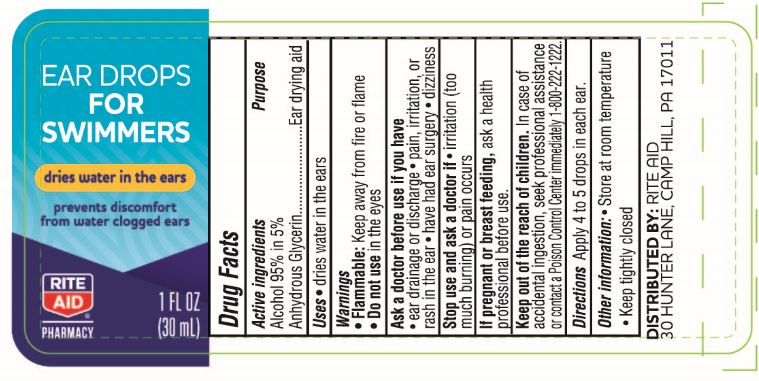 DRUG LABEL: EAR DRYING AGENT
NDC: 11822-1233 | Form: LIQUID
Manufacturer: Rite Aid
Category: otc | Type: HUMAN OTC DRUG LABEL
Date: 20231215

ACTIVE INGREDIENTS: ISOPROPYL ALCOHOL 94.998 g/100 mL
INACTIVE INGREDIENTS: GLYCERIN

Rite Aid Ear Drops for Swimmers

ACTIVE INGREDIENT

Isopropyl Alcohol 95% in 5% Anhydrous Glycerin

PURPOSE

Ear Drying Aid

INDICATIONS AND USAGE

Dries water in the ears

WARNINGS

Flammable: Keep away from fire or flame

Do not use in the eyes

DOSAGE AND ADMINISTRATION

Apply 4 to 5 drops in each affected ear

WHEN USING

Store at room temperature

keep tightly closed

INACTIVE INGREDIENT

Glycerin

Keep out of reach of children. in case of accidental ingestion, seek professional assitance or contact a poison control center immediately. (1-800-222-1222)